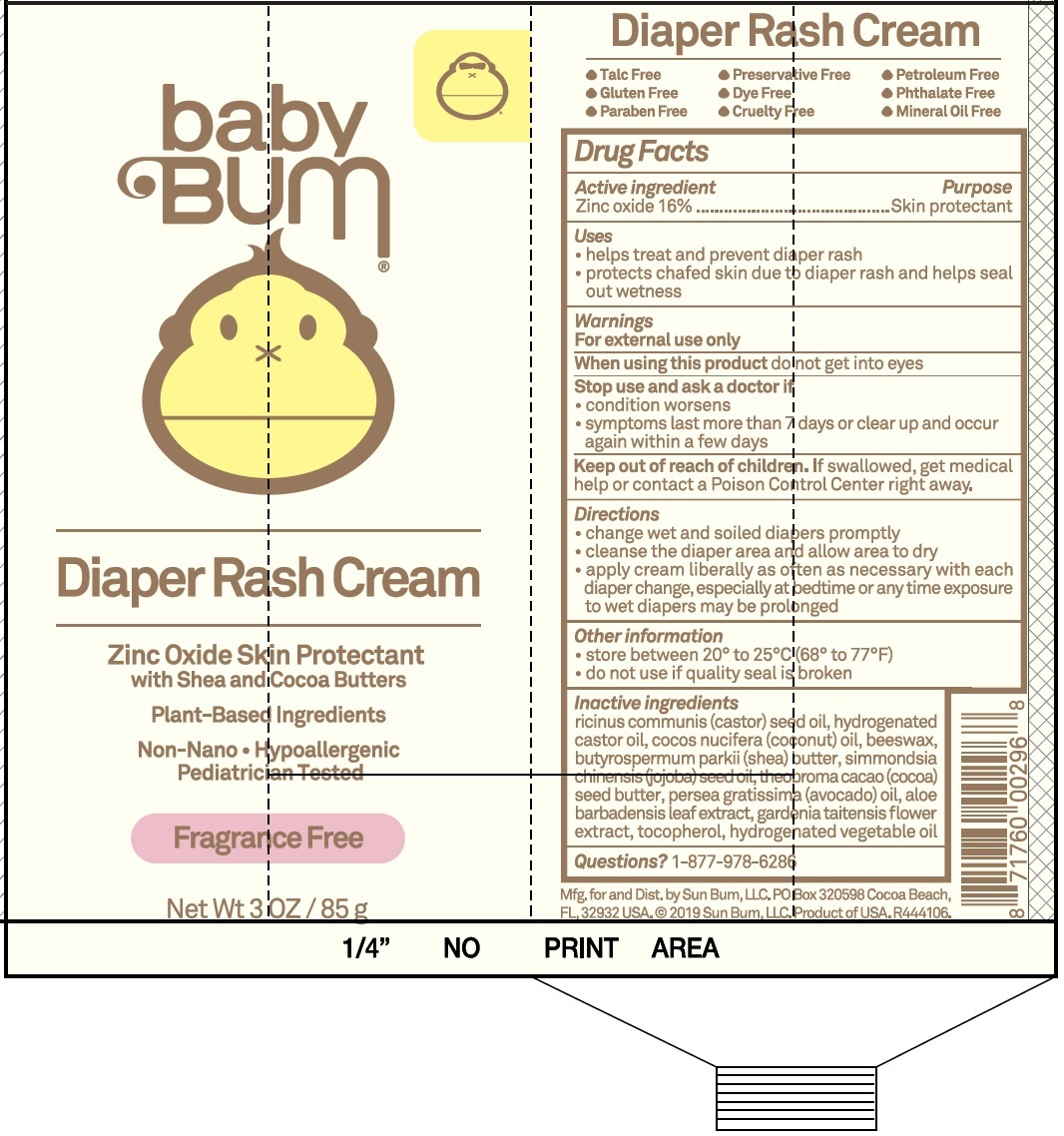 DRUG LABEL: Baby Bum Diaper Rash
NDC: 69039-638 | Form: CREAM
Manufacturer: Sun Bum LLC
Category: otc | Type: HUMAN OTC DRUG LABEL
Date: 20220204

ACTIVE INGREDIENTS: ZINC OXIDE 160 mg/1 g
INACTIVE INGREDIENTS: CASTOR OIL; HYDROGENATED CASTOR OIL; COCONUT OIL; YELLOW WAX; SHEA BUTTER; JOJOBA OIL; COCOA BUTTER; AVOCADO OIL; ALOE VERA LEAF; GARDENIA TAITENSIS FLOWER; TOCOPHEROL

Baby Bum Diaper Rash Cream

Active Ingredients

Zinc oxide 16%

Purpose

Skin protectant

Uses

- helps treat and prevent diaper rash
- protects chafed skin due to diaper rash and helps seal out wetness

Warnings

For external use only

When using this product

do not get into eyes

Stop use and ask a doctor if

- condition worsens
- symptoms last more than 7 days or clear up and occur again withing a few days

Keep out of reach of children.

If swallowed, get medical help or contact a Poison Control Center right away.

Directions

- change wet and soiled diapers promptly
- cleanse the diaper area and allow area to dry
- apply cream liberally as often as necessary with each diaper change, especially at bedtime or any time exposure to wet diapers may be prolonged

Other Information

- store between 20° to 25°C (68° to 77°F)
- do not use if quality seal is broken

Inactive ingredients

ricinus communis (castor) seed oil, hydrogenated castor oil, cocos nucifera (coconut) oil, beeswax, butyrospermum parkii (shea) butter, simmondsia chinensis (jojoba) seed oil, theobroma cacao (cocoa) seed butter, persea gratissima (avocado) oil, aloe barbadensis leaf extract, gardenia taitensis flower extract, tocopherol, hydrogenated vegetable oil

Questions?

1-877-978-6286